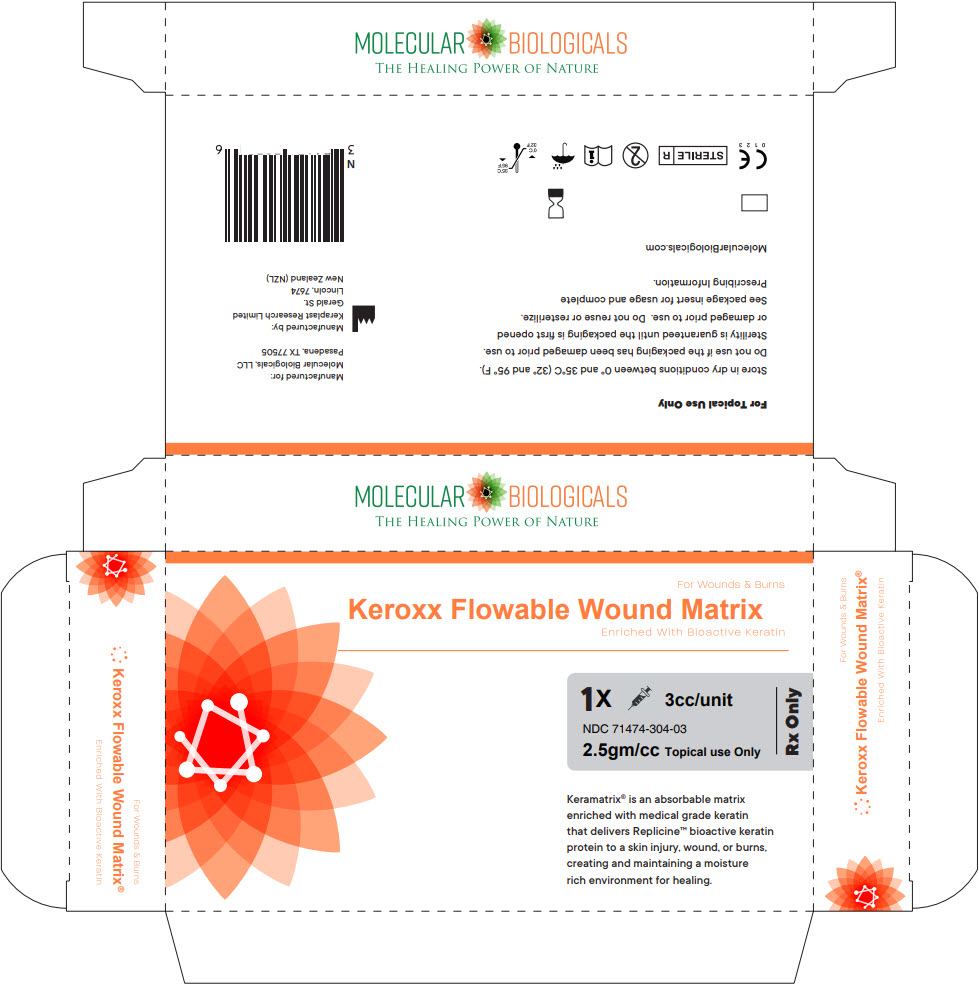 DRUG LABEL: keroxx
NDC: 71474-304 | Form: GEL
Manufacturer: Molecular Biologicals, LLC
Category: other | Type: PRESCRIPTION MEDICAL DEVICE LABEL
Date: 20181130

ACTIVE INGREDIENTS: AMINO ACIDS, HAIR KERATIN 100 mg/1 g

Keroxx®

Flowable Wound Matrix

Rx Prescription Only
Single Use
Topical use Only

STERILE | R

C E
0 1 2 3

CAUTION

Federal (U.S.A.) law restricts this device to sale by or on the order of a physician (or properly licensed Healthcare practitioner).

DESCRIPTION

Keroxx® is an advanced wound care device comprised of a flowable wound matrix.

The flowable wound matrix provides a scaffold for cellular migration, proliferation and capillary growth.

It is supplied in single use kits containing one 3cc syringe with flowable wound matrix and one flexible injector.

INDICATIONS FOR USE

Chronic wounds, surgical wounds, Donor sites/grafts, Diabetic ulcers, chronic ulcers of mixed vascular etiologies, venous stasis ulcers, Pressure ulcers (stages I-IV), partial & full thickness wounds, donor sites/grafts.

DIRECTIONS FOR USE

(NOTE: ALWAYS HANDLE USING ASEPTIC TECHNIQUE)

WOUND BED PREPARATION & APPLICATION | DRESSING CHANGES & REAPPLICATIONS
1. Prepare wound area using standard debridement methods to ensure the wound is free of debris and devitalized tissue. The wound may be surgically debrided to ensure the wound edges contain viable tissue. A small influx of blood may be permitted into the wound. 2. Remove the tip cap from the 3cc syringe. 3. Attach the flexible injector tip securely to the syringe. 4. Slowly dispense Keroxx® Flowable Wound Matrix into the wound area. Avoid pressing tip directly against the wound bed to ensure proper flow of Keroxx® from the flexible injector. For easily visible wound areas a thin 1-3mm film covering is adequate. | 5. After application, use an appropriate non-adherent occlusive dressing. Change dressing as necessary. 6. Frequency of dressing changes typically occur every 2-5 days, or as determined by the healthcare provider. 7. Once wound is cleansed using proper technique Keroxx® Flowable Wound Matrix may be reapplied. 8. Proceed with reapplication of appropriate non-adherent occlusive secondary dressing. 9. If clinical signs of infection, excessive redness, blistering or suspected allergic reaction occurs the Keroxx should not be reapplied and proper notification and documentation should be done.

CONTRADICATIONS

Keroxx® should not be used in patients with known sensitivity to keratin. The device is not indicated for third degree burns.

ACTIVE INGREDIENT: Keratin

PRECAUTIONS

Do not reuse or re-sterilize. Do not use if package is open or tip cap is missing or not fully attached to syringe, or if package is unsealed. Use prior to expiration date.

STORAGE

Do not use if Package has been opened or damaged. Should be stored at a clean, dry location at ambient temperature.

HOW SUPPLIED

Keroxx® is supplied sterile, in single use kits containing one 3cc syringe with flowable wound matrix, one flexible injector.

Keroxx®
3cc syringe/unit
NDC 71474-304-03

Manufactured for:
Molecular Biologicals, LLC
Pasadena, TX 77505 | 1-844-793-9933
By Keraplast Research, Ltd
Gerald St. Lincoln, 7674 NZ

Keroxx® is a registered trademark of Molecular Biologicals, LLC.
The product incorporates patented and /or patent pending technologies owned by Molecular Biologicals, LLC.

Issue Date 01Jan17
DWG005/9

PRINCIPAL DISPLAY PANEL - 3 cc Syringe Box

For Wounds & Burns
Keroxx Flowable Wound Matrix
Enriched With Bioactive Keratin

1X 3cc/unit
NDC 71474-304-03
2.5gm/cc Topical use Only
Rx Only

Keramatrix® is an absorbable matrix
enriched with medical grade keratin
that delivers Replicine™ bioactive keratin
protein to a skin injury, wound, or burns,
creating and maintaining a moisture
rich environment for healing.